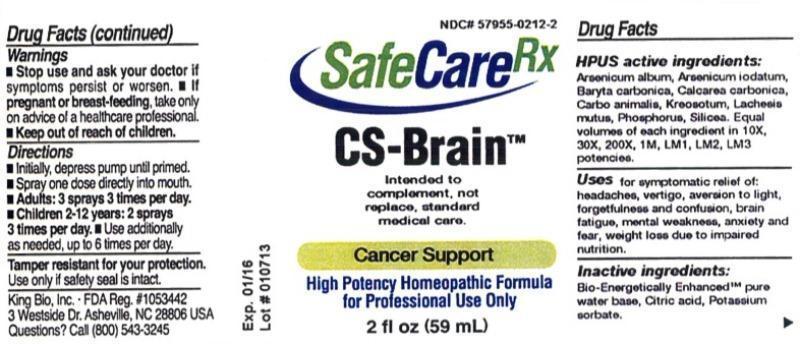 DRUG LABEL: CS-Brain
NDC: 57955-0212 | Form: LIQUID
Manufacturer: King Bio Inc.
Category: homeopathic | Type: HUMAN PRESCRIPTION DRUG LABEL
Date: 20130306

ACTIVE INGREDIENTS: ARSENIC TRIOXIDE 10 [hp_X]/59 mL; ARSENIC TRIIODIDE 10 [hp_X]/59 mL; BARIUM CARBONATE 10 [hp_X]/59 mL; OYSTER SHELL CALCIUM CARBONATE, CRUDE 10 [hp_X]/59 mL; CARBO ANIMALIS 10 [hp_X]/59 mL; WOOD CREOSOTE 10 [hp_X]/59 mL; LACHESIS MUTA VENOM 10 [hp_X]/59 mL; PHOSPHORUS 10 [hp_X]/59 mL; SILICON DIOXIDE 10 [hp_X]/59 mL
INACTIVE INGREDIENTS: WATER; CITRIC ACID MONOHYDRATE; POTASSIUM SORBATE

CS-Brain

Warnings

- Stop use and ask your doctor if symptoms persist or worsen
- If pregnant or breast-feeding, take only on advice of a healthcare professional.
- Keep out of reach of children.

Tamper resistant for your protection. Use only if safety seal is intact.

Keep out of reach of children.

Directions

- Initially, depress pump until primed.
- Spray one dose directly into mouth.
- Adults: 3 sprays 3 times per day.
- Children 2-12 years: 2 sprays 3 times per day
- Use additionally as needed, up to 6 times per day.

HPUS Active Ingredients

Arsenicum album, Arsenicum iodatum, Baryta carbonica, Calcarea carbonica, Carbo animalis, Kreosotum, Lachesis mutus, Phosphorus and Silicea.

Equal volumes of each ingredient in 10X, 30X, 200X, 1M, LM1, LM2, LM3 potencies.

Purpose

Uses for symptomatic relief of:

- headaches
- vertigo
- aversion to light
- forgetfulness and confusion
- brain fatigue
- mental weakness
- anxiety and fear
- weight loss due to impaired nutrition

Inactive Ingredients

Bio-Energetically Enhanced™ pure water base, Citric acid, Potassium sorbate

Indications and Usage

Uses for symptomatic relief of: headaches, vertigo, aversion to light, forgetfulness and confusion, brain fatigue, mental weakness, anxiety and fear, weight loss due to impaired nutrition.